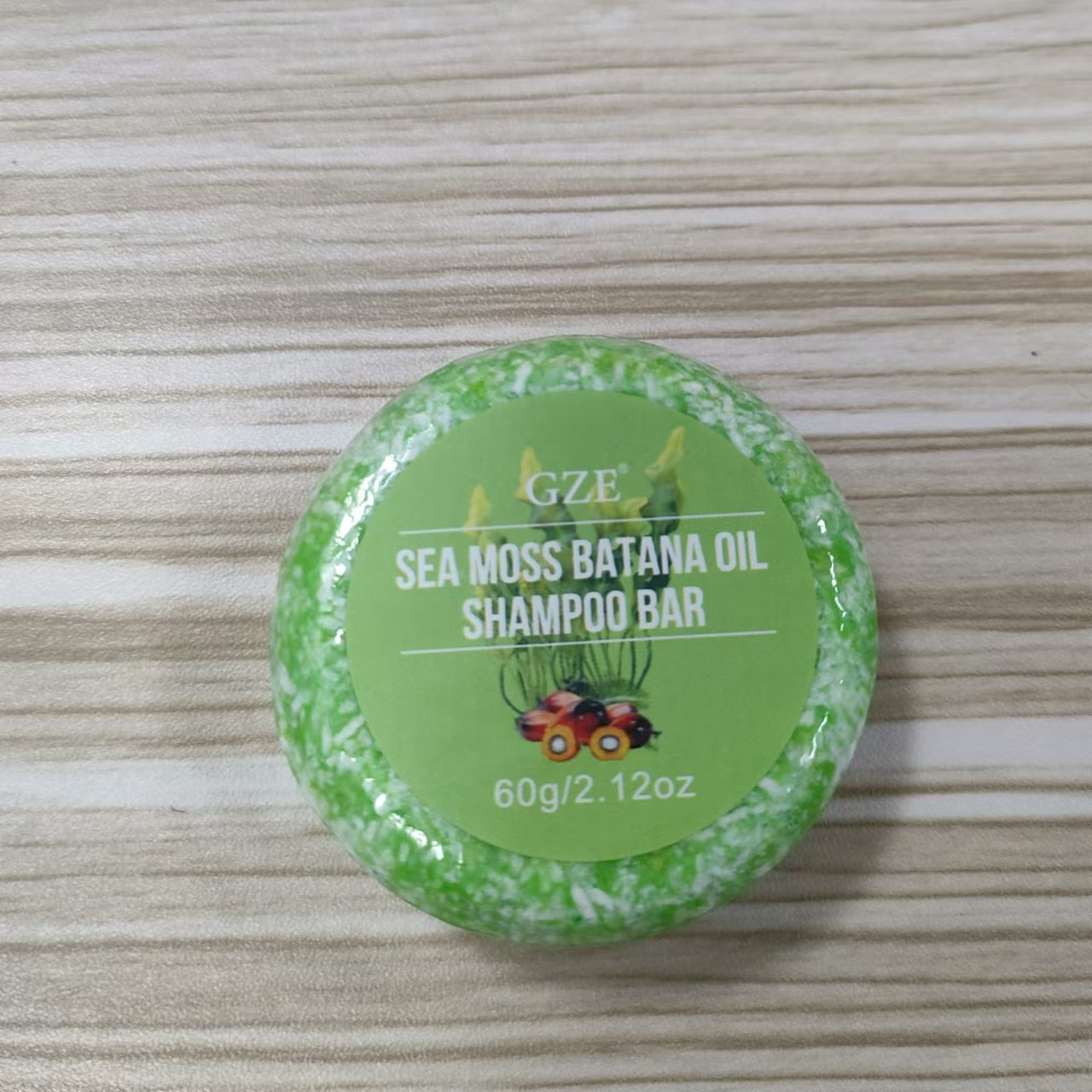 DRUG LABEL: GZE Sea Moss Batana Oil ShampooBar
NDC: 74458-261 | Form: SOAP
Manufacturer: Guangzhou Yilong Cosmetics Co., Ltd
Category: otc | Type: HUMAN OTC DRUG LABEL
Date: 20241028

ACTIVE INGREDIENTS: CHONDRUS CRISPUS CARRAGEENAN 5 g/100 g; ELAEIS GUINEENSIS (PALM) OIL 5 g/100 g
INACTIVE INGREDIENTS: HYDROGENATED CASTOR OIL; GLYCERIN

GZE SEA MOSS BATANA OIL SHAMPOO BAR

ACTIVE INGREDIENT

Chondrus Crispus Extract

Elaeis Guineensis (Palm) Oil

INACTIVE INGREDIENT

Glycerin

Hydrogenated Castor Oil

PURPOSE

Cleanses the scalp and strengthens the hair shaft.

INDICATIONS AND USAGE

After you’ve wet your hair, take shampoo bar and either rub the bar between your hands and massage the lather into your hair. Rinse as you’d normally do and repeat as desired.

WARNINGS

For external use only.

Stop use and ask a doctor if rash occurs.

Do not use on damaged or broken skin.

When using this product keep out of eyes. Rinse with water to remove.

Keep out of reach of children. If swallowed, get medical help or contact a Poison Control Center right away.

DOSAGE AND ADMINISTRATION

After you’ve wet your hair, take shampoo bar and either rub the bar between your hands and massage the lather into your hair. Rinse as you’d normally do and repeat as desired.